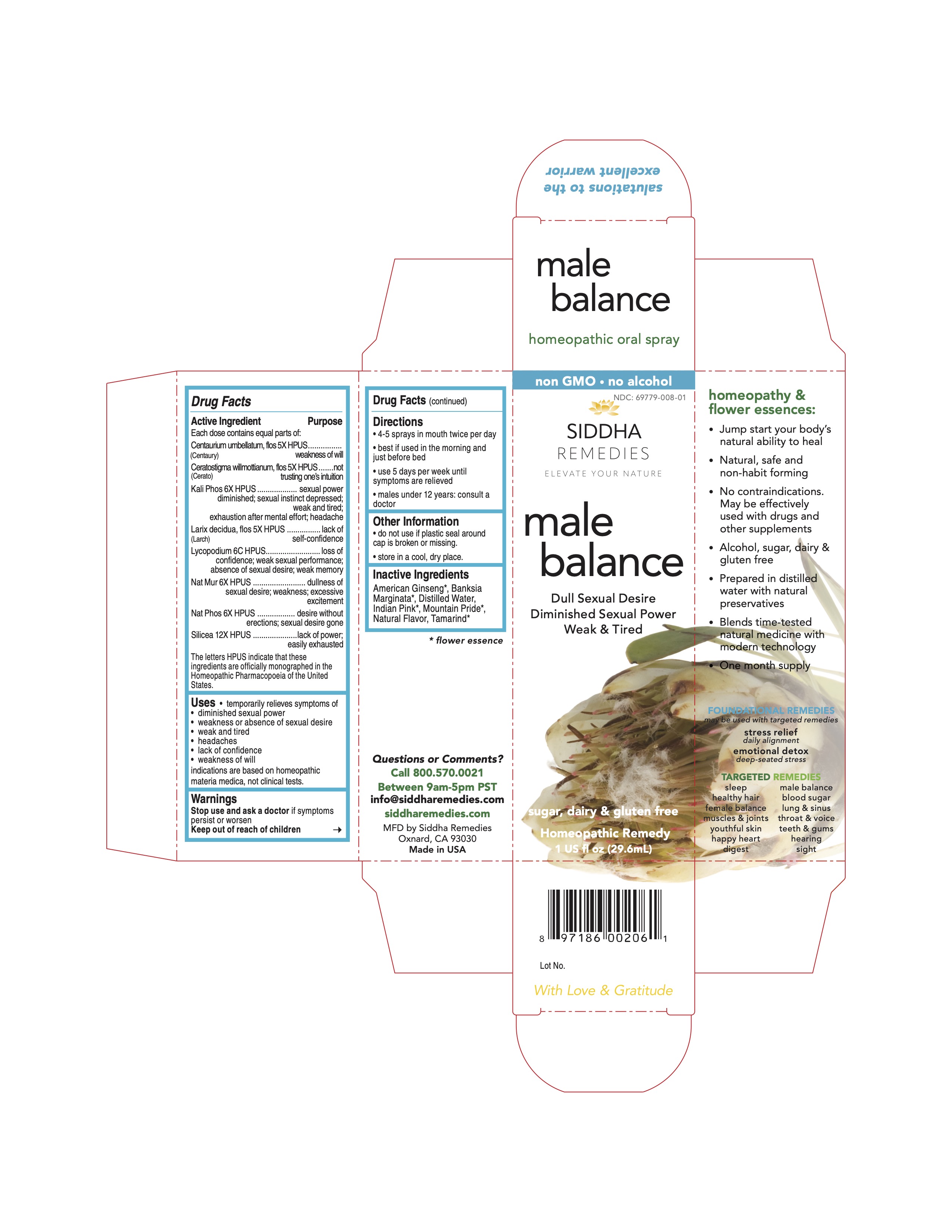 DRUG LABEL: male balance
NDC: 69779-008 | Form: SPRAY
Manufacturer: Siddha Flower Essences LLC
Category: homeopathic | Type: HUMAN OTC DRUG LABEL
Date: 20251231

ACTIVE INGREDIENTS: CENTAURIUM ERYTHRAEA FLOWER 5 [hp_X]/29.6 mL; CERATOSTIGMA WILLMOTTIANUM FLOWER 5 [hp_X]/29.6 mL; POTASSIUM PHOSPHATE, DIBASIC 6 [hp_X]/29.6 mL; LARIX DECIDUA FLOWERING TOP 5 [hp_X]/29.6 mL; LYCOPODIUM CLAVATUM SPORE 6 [hp_C]/29.6 mL; SODIUM CHLORIDE 6 [hp_X]/29.6 mL; SODIUM PHOSPHATE, DIBASIC, HEPTAHYDRATE 6 [hp_X]/29.6 mL; SILICON DIOXIDE 12 [hp_X]/29.6 mL
INACTIVE INGREDIENTS: AMERICAN GINSENG; WATER; TAMARIND

Drug Facts

Active Ingredient

Each dose contains equal parts of:

Centaurium umbellatum, flos (Centaury) 5X HPUS
Ceratostigma willmottianum, flos (Cerato) 5X HPUS
Kali Phos 6X HPUS
Larix decidua, flos (Larch) 5X HPUS
Lycopodium 6C HPUS
Nat Mur 6X HPUS
Nat Phos 6X HPUS
Silicea 12X HPUS

Purpose

Each dose contains equal parts of:
Centaurium umbellatum, flos (Centaury) 5X HPUS............weakness of will
Ceratostigma willmottianum, flos (Cerato) 5X HPUS..........not trusting one's intuition
Kali Phos 6X HPUS........................................................sexual power diminished; sexual instinct depressed; weak and tired; exhaustion after mental effort; headache
Larix decidua, flos (Larch) 5X HPUS................................lack of self-confidence
Lycopodium 6C HPUS....................................................loss of confidence; weak sexual performance; absence of sexual desire; weak memory
Nat Mur 6X HPUS..........................................................dullness of sexual desire; weakness; excessive excitement
Nat Phos 6X HPUS........................................................desire without erections; sexual desire is gone
Silicea 12X HPUS..........................................................lack of power; easily exhausted
The letters HPUS indicate that these ingredients are officially monographed in the Homeopathic Pharmacopoeia of the United States.

Uses

- temporarily relieves symptoms of
- diminished sexual power
- weakness or absence of sexual desire
- weak and tired
- headaches
- lack of confidence
- weakness of will

indications are based on homeopathic materia medica, not clinical tests.

Warnings

Stop use and ask a doctor if symptoms persist or worsen

Keep out of reach of children

Directions

- 4-5 sprays in mouth twice per day
- best if used in the morning and just before bed
- use 5 days a week until symptoms are relieved
- males under 12 years: consult a doctor

Other Information

- do not use if plastic seal around cap is broken
- store in a cool, dry place

Inactive Ingredients

American Ginseng*, Banksia Marginata*, Indian Pink*, Mountain Pride*, Natural Flavor, Purified Water, Tamarind*

*flower essence

Questions or Comments?

Call 800.570.0021
Between 9am-5pm PST
info@siddhaflowers.com
siddhaflowers.com

MFD by Siddha Flower Essences
Oxnard, CA 93030

Made in USA

Side Panel

homeopathy and flower essences:

- Jump start your body's natural ability to heal
- Natural, safe, and non-habit forming
- No contraindications. May be effectively used with drugs and other supplements
- Alcohol, sugar, dairy and gluten free
- Prepared in purified water with natural preservatives
- Blends time-tested natural medicine with modern technology
- One month supply

FOUNDATIONAL REMEDIES
may be used with targeted remedies

stress relief
daily alignment
emotional detox
deep-seated stress

TARGETED REMEDIES

sleep male balance
healthy hair blood sugar
female balance lung and sinus
muscles and joints throat and voice
youthful skin teeth and gums
happy heart hearing
digest sight

Principal Display Panel

non GMO - no alcohol
siddha cell salts + flower essences
male balance
Dull Sexual Desire
Diminished Sexual Power
Weak and Tired
sugar, dairy and gluten free
Homeopathic Remedy
1 US fl oz (29.6mL)